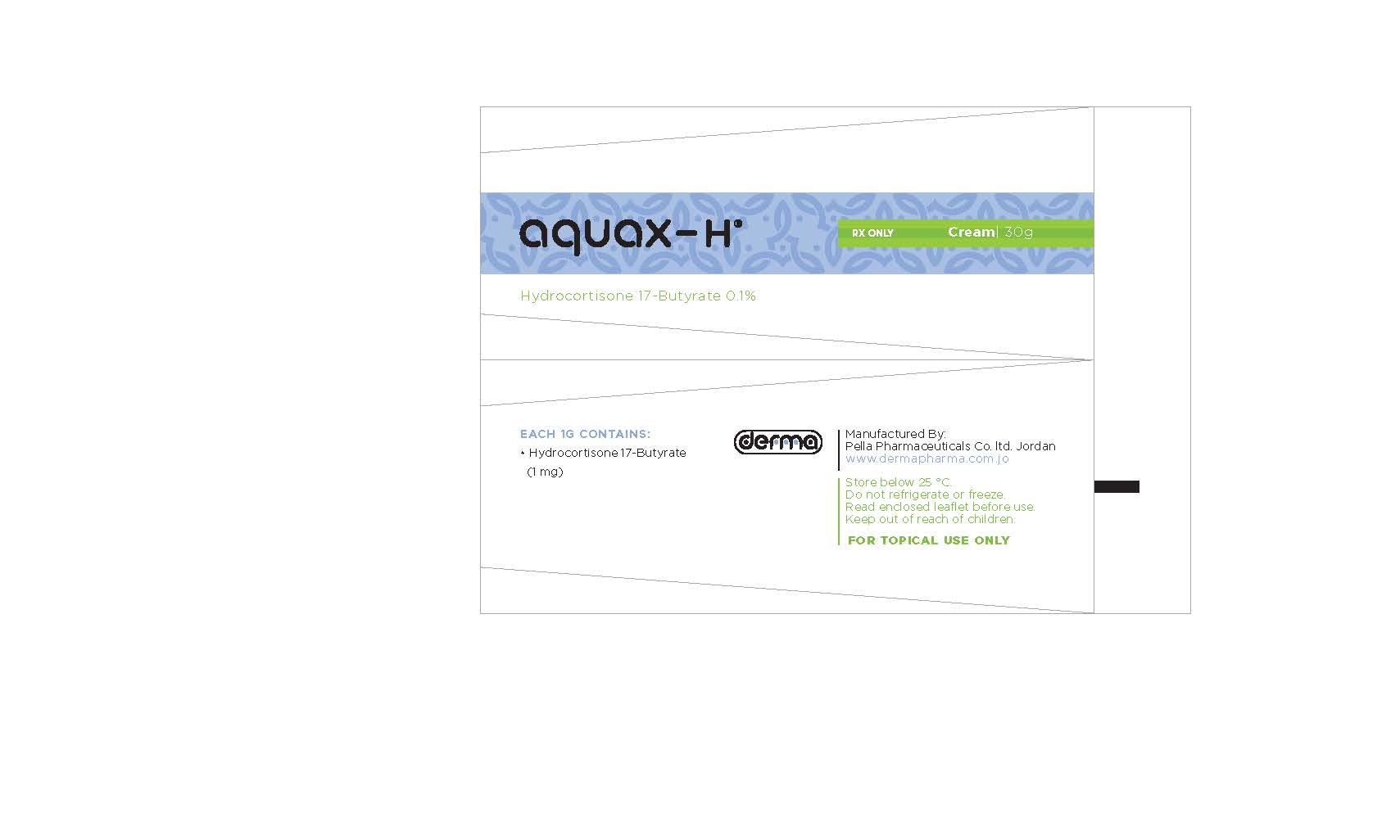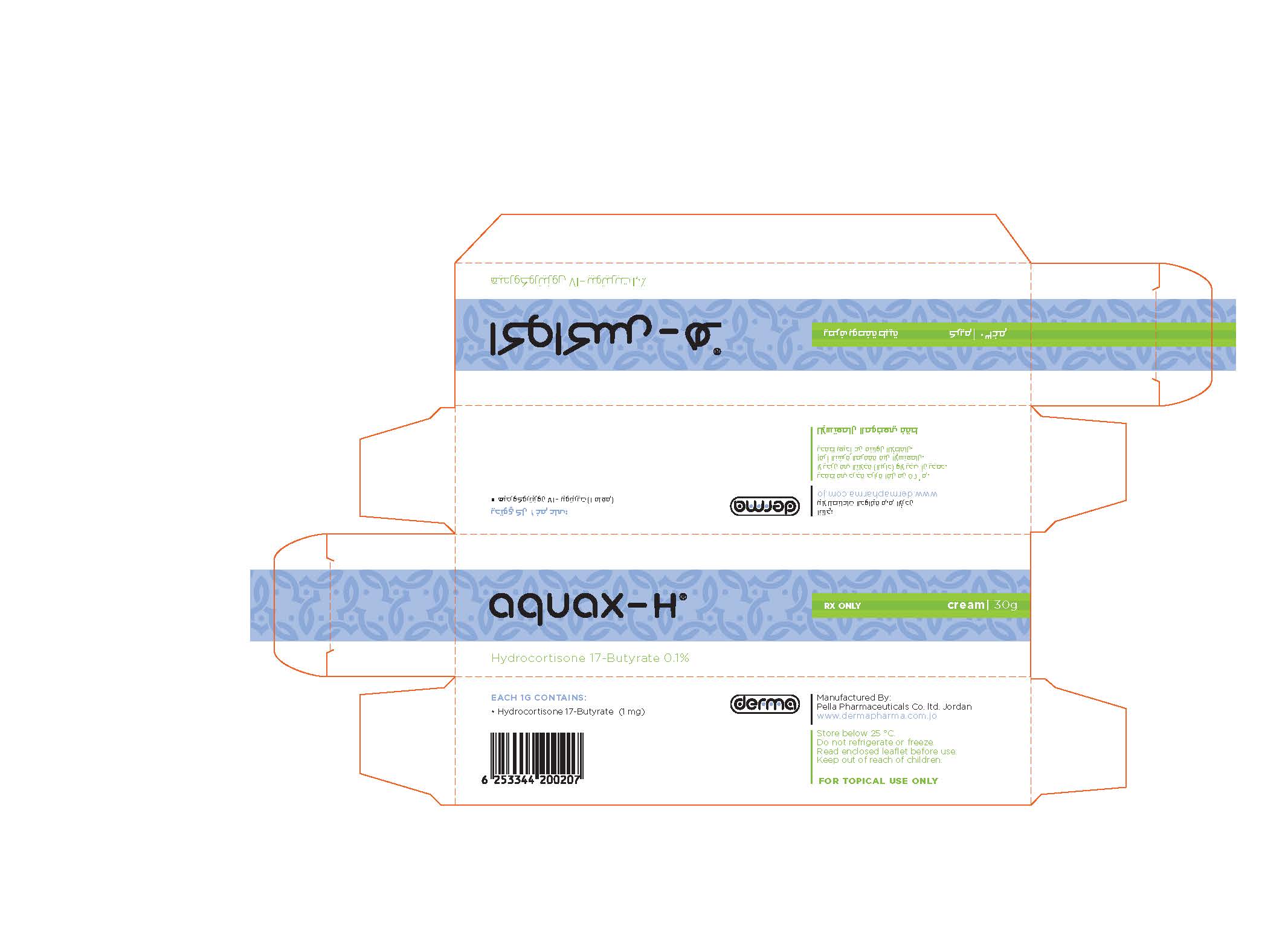 DRUG LABEL: Aquax-H
NDC: 82160-127 | Form: CREAM
Manufacturer: Pella Pharmaceuticals Co. ltd
Category: prescription | Type: HUMAN PRESCRIPTION DRUG LABEL
Date: 20241231

ACTIVE INGREDIENTS: HYDROCORTISONE BUTYRATE 30 mg/30 g

Aquax-H

Composition

Each 1 g contains: Hydrocortisone 17-Butyrate 1 mg.
Excipients: Petrolatum, Cetearyl Alcohol, Mineral Oil, Ceteareth-20, Benzyl Alcohol, Citric Acid, Sodium Citrate, Propylparaben and Purified Water.

Properties

Aquax-H® Cream contains a corticosteroid and quickly suppresses symptoms of certain skin conditions such as itching, redness and scaling. Corticosteroids don't generally remove the cause of the symptoms. The Aquax-H® Cream base ensures that the skin condition becomes less moist.

Indications

Aquax-H® Cream can be used for the treatment of superficial skin conditions where itching, redness and scaling are often present.

Contraindications

Do not use Aquax-H® Cream

- If your skin condition is caused by infections with bacteria, viruses, fungi, yeasts or parasites as these could either be made worse or become unnoticeable.
- In acne even if the skin is red.
- For wounds or scaly skin (ichthyosis).
- If your skin condition is the result of earlier treatment with corticosteroids such as inflammation of the skin around the mouth or thin skin possibly with streaks and vulnerable blood vessels.
- For childhood rash on the foot sole.
- If you are hypersensitive to hydrocortisone 17-butyrate or to any of the excipients (uncommon).

Precautions

Aquax-H®Cream contains certain excipients like Cetearyl Alcohol that in rare cases can cause hypersensitivity reactions (itching, red spots) of the skin.

Drug Interactions

Inform your doctor or pharmacist if you are using other medicines or have used them in the recent past. This also applies to medicines you have obtained without a prescription

Warnings

Be extra careful with Aquax-H® Cream

- If you want to treat the facial skin, genital skin and skin folds as these areas of skin are particularly sensitive to corticosteroids.
- If you apply the cream under an occlusive bandage, to large areas of skin or are treating a child in which cases you should be under the control of your doctor.
- The Aquax-H® Cream should not be introduced into the eye or applied to the eyelids.
- The application of corticosteroids for long periods in children should be avoided.
- Consult your doctor if any of the above warnings apply to you.

Pregnancy

Ask your doctor or pharmacist for advice before using a medical product. If you want to apply the cream during pregnancy then discuss this with your doctor.

Breast-feeding

Ask your doctor or pharmacist for advice before using a medical product. If you want to apply the Aquax-H® during breast-feeding then discuss this with your doctor.

Driving and the use of machines

There is nothing known about Aquax-H®Cream and the ability to drive or to use machines. However, no effects are to be expected.

Dosage and Administration

Apply Aquax-H® Cream thinly to the affected skin area and massage lightly into the skin. Do not apply more often than 1-3 times daily unless your doctor has advised otherwise.
When your symptoms have receded, your doctor may decide that you can use the cream less often. In general, you should not use more than 1 to 2 tubes per week.
What you can expect when treatment has been stopped
The original symptoms can reappear if treatment is stopped prematurely.
Always consult you doctor or pharmacist before stopping treatment.

Overdosage

What you should do if you have used too much Aquax-H Cream
Contact you doctor or pharmacist if you have used too much Aquax-H® Cream.
What you should do if you have forgotten to use Aquax-H Cream
If you have forgotten to apply it a single time just carry on as before. There is no need to compensate for a missed application.

Side Effects

Aquax-H® Cream can cause side effects just like all medicines.
You could sometimes have a burning or prickly feeling at the site of application but this is mostly not serious and disappears on its own.
If you have used it for prolonged periods or under an occlusive bandage, you could get a rash, pimples or the formation of pus. The skin could become discolored or thin, sometimes with stripes.
Consult your doctor if you have any of these side effects.
Also consult your doctor or pharmacist if you either have any side effects not mentioned in this leaflet or any others that you think might be serious.

Storage

Store below 25 °C
Do not store in a refrigerator or freezer.

How Supplied

30 g packs

THIS IS A MEDICAMENT

- Medicament is a product which affects your health and its consumption contrary to instructions is dangerous for you.
- Strictly follow the doctor's prescription, the method of use and the instruction of the pharmacist who sold the medicament.
- The doctor and the pharmacist are experts in medicine, its benefits and risks.
- Do not by yourself interrupt the period of treatment prescribed for you.
- Do not repeat the same prescription without consulting your doctor.
- Keep medicament out of reach of children.